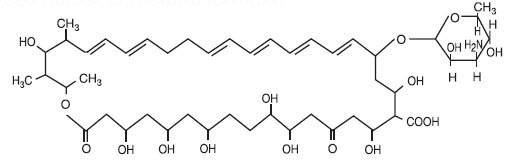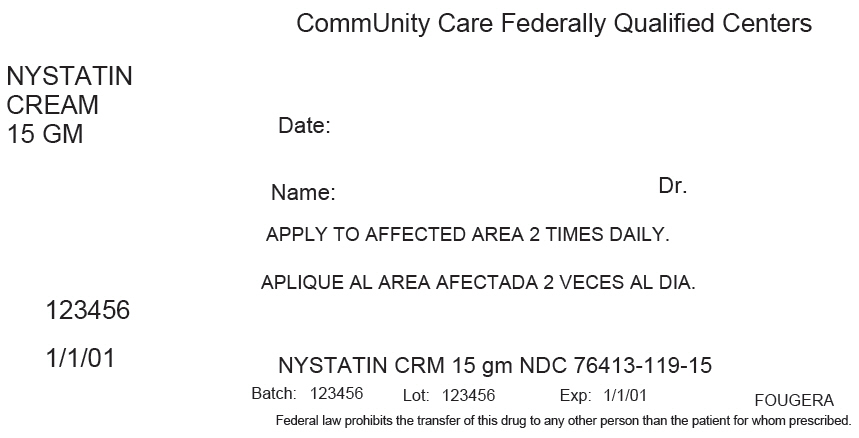 DRUG LABEL: nystatin
NDC: 76413-119 | Form: CREAM
Manufacturer: Central Texas Community Health Centers
Category: prescription | Type: HUMAN PRESCRIPTION DRUG LABEL
Date: 20160125

ACTIVE INGREDIENTS: nystatin 100000 [USP'U]/1 g
INACTIVE INGREDIENTS: Polysorbate 60; Algeldrate; Titanium Dioxide; Glyceryl Monostearate; PEG-8 Stearate; Silicon Dioxide; Sorbic Acid; Propylene Glycol; Ethylenediamine; Sorbitol; Methylparaben; Propylparaben; Hydrochloric Acid; Petrolatum; Water

NYSTATIN CREAM USP

FOR TOPICAL USE ONLY.

Rx only

NOT FOR OPHTHALMIC USE.

DESCRIPTION:

Nystatin is a polyene antifungal antibiotic obtained from Streptomyces nursei. Structural formula:

Molecular Weight 926.13

Molecular Formula C47H75NO17

Nystatin cream is for dermatologic use.

Nystatin cream for topical use, contains 100,000 USP nystatin units per gram in an aqueous, vanishing cream base containing Polysorbate 60, Aluminum Hydroxide Compressed Gel, Titanium Dioxide, Glyceryl Monostearate, Polyethylene Glycol 400 Monostearate, Simethicone Emulsion, Sorbic Acid, Propylene Glycol, Ethylenediamine, Polyoxyethylene Fatty Alcohol Ether, Sorbitol Solution, Methylparaben, Propylparaben, Hydrochloric Acid, White Petrolatum, and Purified Water.

CLINICAL PHARMACOLOGY:

PHARMACOKINETICS

Pharmacokinetics: Nystatin is not absorbed from intact skin or mucous membrane.

MICROBIOLOGY

Microbiology: Nystatin is an antifungal antibiotic which is both fungistatic and fungicidal in vitro against a wide variety of yeasts and yeast-like fungi, including Candida albicans, C. parapsilosis, C. tropicalis, C. guilliermondi, C. pseudotropicalis, C. krusei, Torulopsis glabrata, Tricophyton rubrum, T. mentagrophytes. Nystatin acts by binding to sterols in the cell membrane of susceptible species resulting in a change in membrane permeability and the subsequent leakage of intracellular components. On repeated subculturing with increasing levels of nystatin, Candida albicans does not develop resistance to nystatin. Generally, resistance to nystatin does not develop during therapy. However, other species of Candida (C. tropicalis, C. guilliermondi, C. krusei, and C. stellatoides) become quite resistant on treatment with nystatin and simultaneously become cross resistant to amphotericin as well. This resistance is lost when the antibiotic is removed. Nystatin exhibits no appreciable activity against bacteria, protozoa, or viruses.

INDICATIONS AND USAGE:

Nystatin cream is indicated in the treatment of cutaneous or mucocutaneous mycotic infections caused by Candida albicans and other susceptible Candida species.

This cream is not indicated for systemic, oral, intravaginal or ophthalmic use.

CONTRAINDICATIONS:

Nystatin cream is contraindicated in patients with a history of hypersensitivity to any of their components.

PRECAUTIONS:

GENERAL PRECAUTIONS

General: Nystatin cream should not be used for the treatment of systemic, oral, intravaginal or ophthalmic infections.

If irritation or sensitization develops, treatment should be discontinued and appropriate measures taken as indicated. It is recommended that KOH smears, cultures, or other diagnostic methods be used to confirm the diagnosis of cutaneous or mucocutaneous candidiasis and to rule out infection caused by other pathogens.

INFORMATION FOR THE PATIENT: Patients using this medication should receive the following information and instructions:

1. The patient should be instructed to use this medication as directed (including the replacement of missed doses). This medication is not for any disorder other than that for which it is prescribed.

2. Even if symptomatic relief occurs within the first few days of treatment, the patient should be advised not to interrupt or discontinue therapy until the prescribed course of treatment is completed.

3. If symptoms of irritation develop, the patient should be advised to notify the physician promptly.

LABORATORY TESTS

Laboratory Tests: If there is a lack of therapeutic response, KOH smears, cultures, or other diagnostic methods should be repeated.

CARCINOGENESIS AND MUTAGENESIS AND IMPAIRMENT OF FERTILITY

Carcinogenesis, Mutagenesis, Impairment of Fertility: No long-term animal studies have been performed to evaluate the carcinogenic potential of nystatin. No studies have been performed to determine the mutagenicity of nystatin or the effects on male or female fertility.

PREGNANCY

TERATOGENIC EFFECTS

Pregnancy: Teratogenic Effects: Category C: Animal reproduction studies have not been conducted with any nystatin cream. It also is not known whether this cream can cause fetal harm when used by a pregnant woman or can affect reproductive capacity. Nystatin cream should be prescribed for a pregnant woman only if the potential benefit to the mother outweighs the potential risk to the fetus.

NURSING MOTHERS

Nursing Mothers: It is not known whether nystatin is excreted in human milk. Caution should be exercised when nystatin is prescribed for a nursing woman.

PEDIATRIC USE

Pediatric Use: Safety and effectiveness have been established in the pediatric population from birth to 16 years. (See DOSAGE AND ADMINISTRATION.)

GERIATRIC USE

Geriatric Use: Clinical studies with nystatin cream did not include sufficient numbers of subjects aged 65 years and older to determine whether they respond differently than younger subjects. Other reported clinical experience has not identified differences in responses between elderly and younger patients, but greater sensitivity of some older individuals cannot be ruled out.]

ADVERSE REACTIONS:

The frequency of adverse events reported in patients using nystatin cream is less than 0.1%. The more common events that were reported include allergic reactions, burning, itching, rash, eczema, and pain on application. (See PRECAUTIONS: General.)

DOSAGE AND ADMINISTRATION:

Adults and Pediatric Patients (Neonates and Older): Apply liberally to affected area twice daily or as indicated until healing is complete.

HOW SUPPLIED:

Nystatin Cream USP is available as follows:

NDC 0168-0054-15 15 gram tube
NDC 0168-0054-30 30 gram tube

Each tube provides 100,000 USP Nystatin Units per gram.

Store at 20°-25°C (68°-77°F) [see USP Controlled Room Temperature].

Avoid freezing.

E. FOUGERA & CO.
A division of
Fougera
PHARMACEUTICALS INC.
Melville, New York 11747

I25415G
R07/13
#61

PRINCIPAL DISPLAY PANEL - 15 GM Tube Carton Label

CommUnity Care Federally Qualified Centers

NYSTATIN
CREAM
15 GM

Date:

Name:
Dr.

APPLY TO AFFECTED AREA 2 TIMES DAILY.

123456

1/1/01

NYSTATIN CRM 15 gm NDC 76413-119-15
Batch: 123456
Lot: 123456
Exp: 1/1/01
FOUGERA
Federal law prohibits the transfer of this drug to any other person than the patient for whom prescribed.